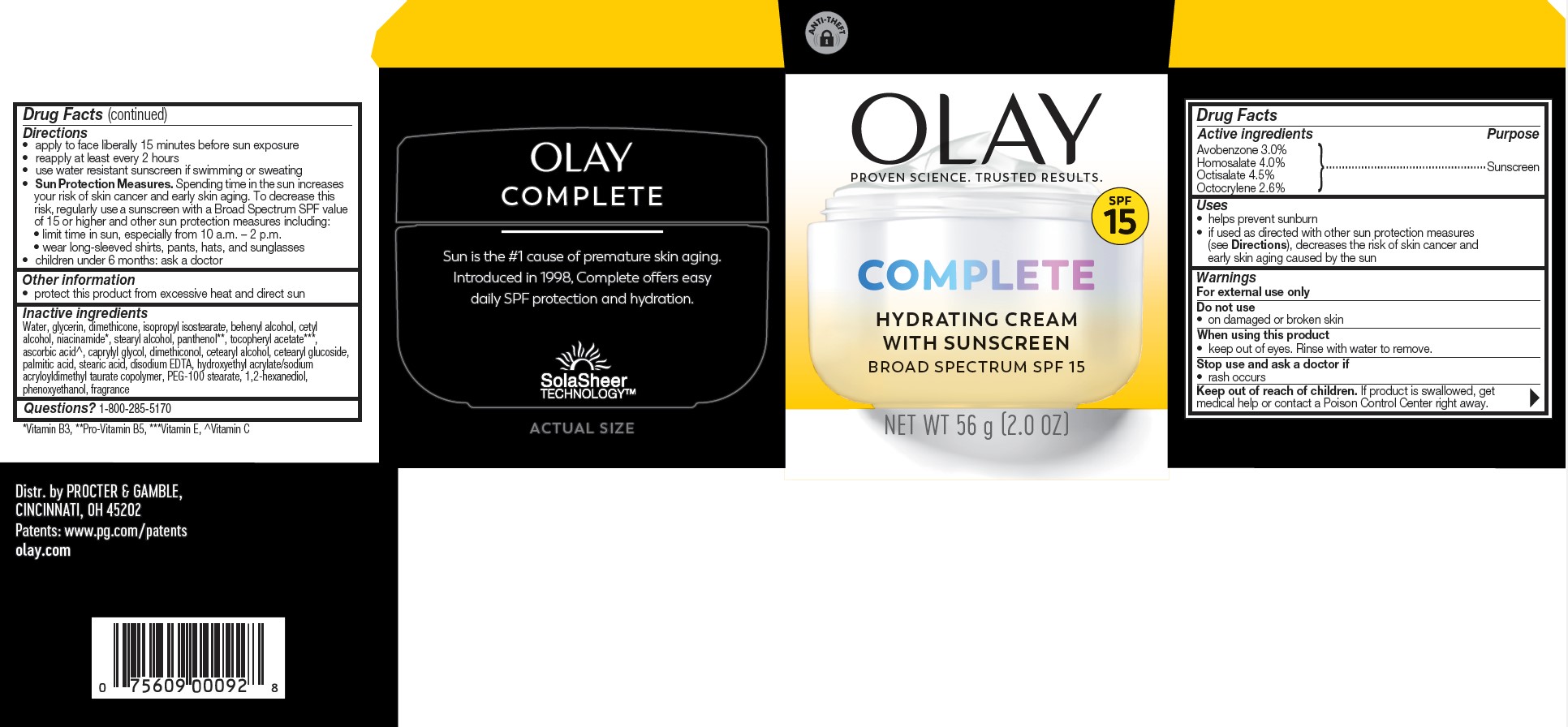 DRUG LABEL: Olay Complete Hydrating with Sunscreen Broad Spectrum SPF 15
NDC: 84126-164 | Form: CREAM
Manufacturer: The Procter & Gamble Manufacturing Company
Category: otc | Type: HUMAN OTC DRUG LABEL
Date: 20250820

ACTIVE INGREDIENTS: AVOBENZONE 3 g/100 g; HOMOSALATE 4 g/100 g; OCTISALATE 4.5 g/100 g; OCTOCRYLENE 2.6 g/100 g
INACTIVE INGREDIENTS: PANTHENOL; .ALPHA.-TOCOPHEROL ACETATE; CETEARYL GLUCOSIDE; CETEARYL ALCOHOL; ASCORBIC ACID; STEARIC ACID; EDETATE DISODIUM; PEG-100 STEARATE; PALMITIC ACID; HYDROXYETHYL ACRYLATE/SODIUM ACRYLOYLDIMETHYL TAURATE COPOLYMER (100000 MPA.S AT 1.5%); 1,2-HEXANEDIOL; PHENOXYETHANOL; ISOPROPYL ISOSTEARATE; CAPRYLYL GLYCOL; WATER; GLYCERIN; DIMETHICONE; NIACINAMIDE; CETYL ALCOHOL; STEARYL ALCOHOL; BEHENYL ALCOHOL; DIMETHICONOL (50000 CST)

Olay Complete Hydrating Cream with Sunscreen Broad Spectrum SPF 15

Drug Facts

ACTIVE INGREDIENT

Sunscreen

PURPOSE

Avobenzone 3.0%
Homosalate 4.0%
Octisalate 4.5%
Octocrylene 2.6%

Uses

- helps prevent sunburn
- if used as directed with other sun protection measures (see Directions), decreases the risk of skin cancer and early skin aging caused by the sun

Warnings

For external use only

Do not use on damaged or broken skin

When using this product keep out of eyes. Rinse with water to remove.

Stop use and ask a doctor if rash occurs

Keep out of reach of children. If product is swallowed, get medical help or contact a Poison Control Center right away.

Directions

- apply liberally 15 minutes before sun exposure
- reapply at least every 2 hours
- use water resistant sunscreen if swimming or sweating
- Sun Protection Measures. Spending time in the sun increases your risk of skin cancer and early skin aging. To decrease this risk, regularly use a sunscreen with a Broad Spectrum SPF value of 15 or higher and other sun protection measures including:
  - limit time in sun, especially from 10 a.m. – 2 p.m.
  - wear long-sleeved shirts, pants, hats, and sunglasses
- children under 6 months: ask a doctor

Other information

- protect this product from excessive heat and direct sun

Inactive ingredients

Water, glycerin, dimethicone, isopropyl isostearate, behenyl alcohol, cetyl alcohol, niacinamide, stearyl alcohol, panthenol, tocopheryl acetate, ascorbic acid, caprylyl glycol, dimethiconol, cetearyl alcohol, cetearyl glucoside, palmitic acid, stearic acid, disodium EDTA, hydroxyethyl acrylate/sodium acryloyldimethyl taurate copolymer, PEG-100 stearate, 1,2-hexanediol, phenoxyethanol, fragrance

Questions or comments?

Call 1-800-285-5170

Dist. by PROCTER & GAMBLE,
CINCINNATI, OH 45202

PRINCIPAL DISPLAY PANEL - 56 g Jar Carton

OLAY

COMPLETE

HYDRATING CREAM

WITH SUNSCREEN

BROAD SPECTRUM SPF 15

NET WT 56g (2.0 OZ)